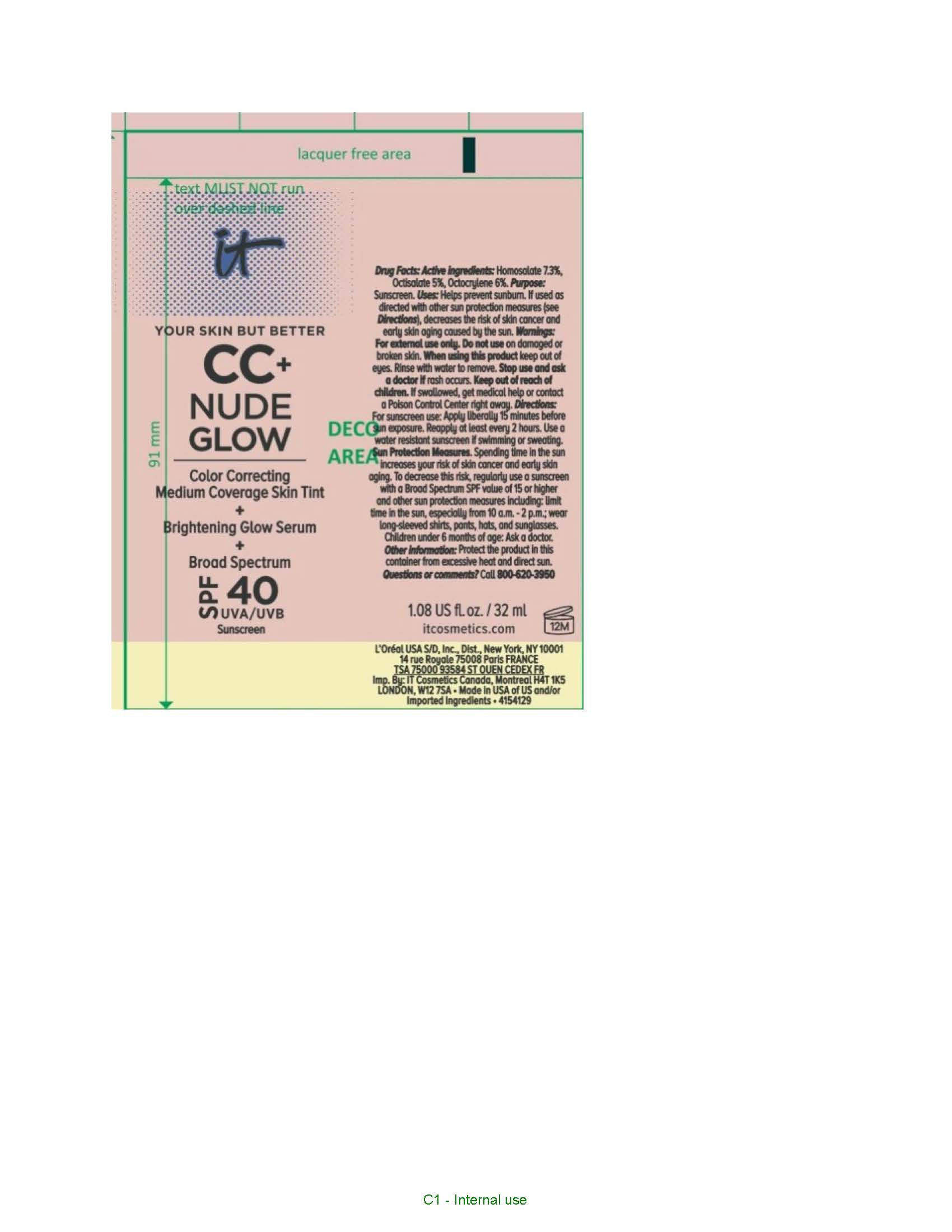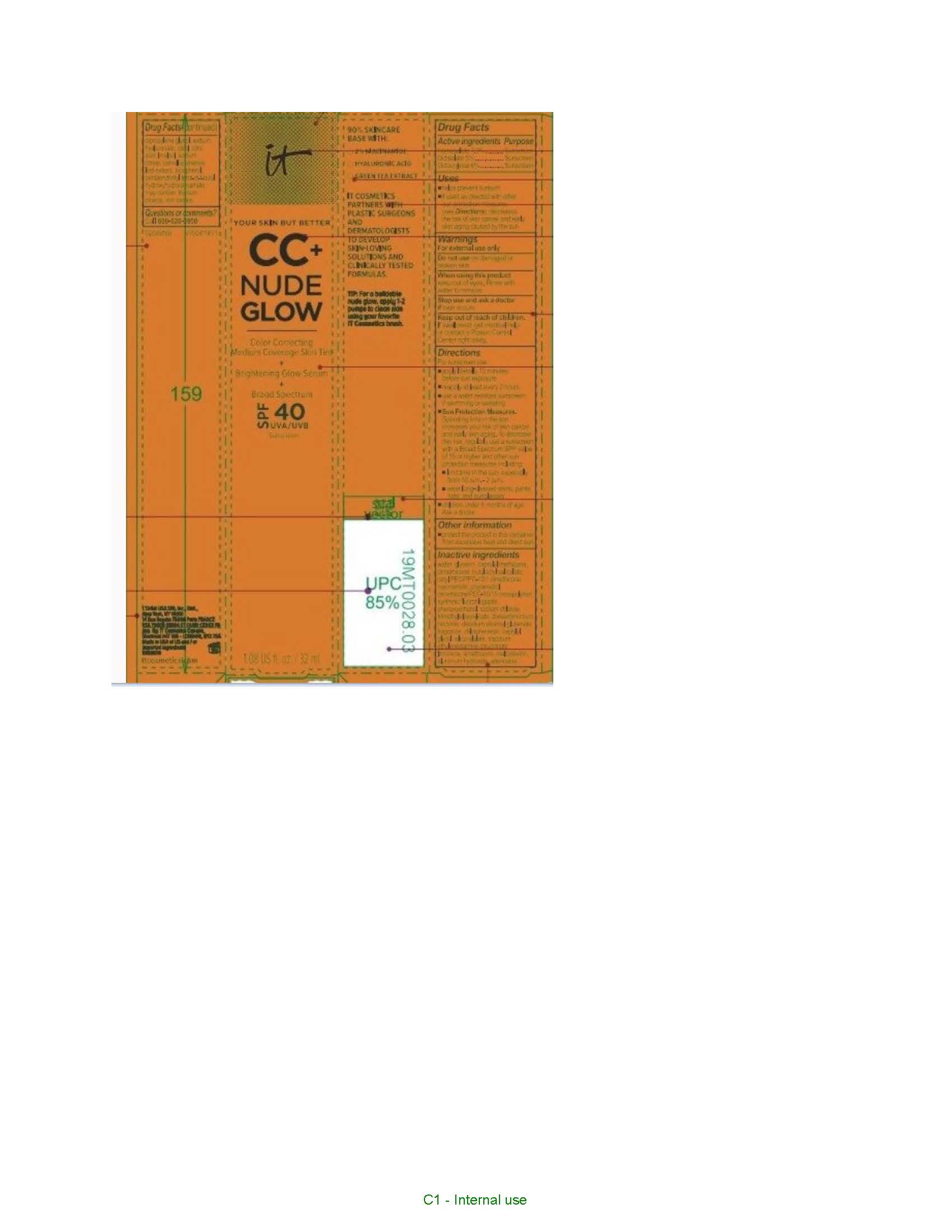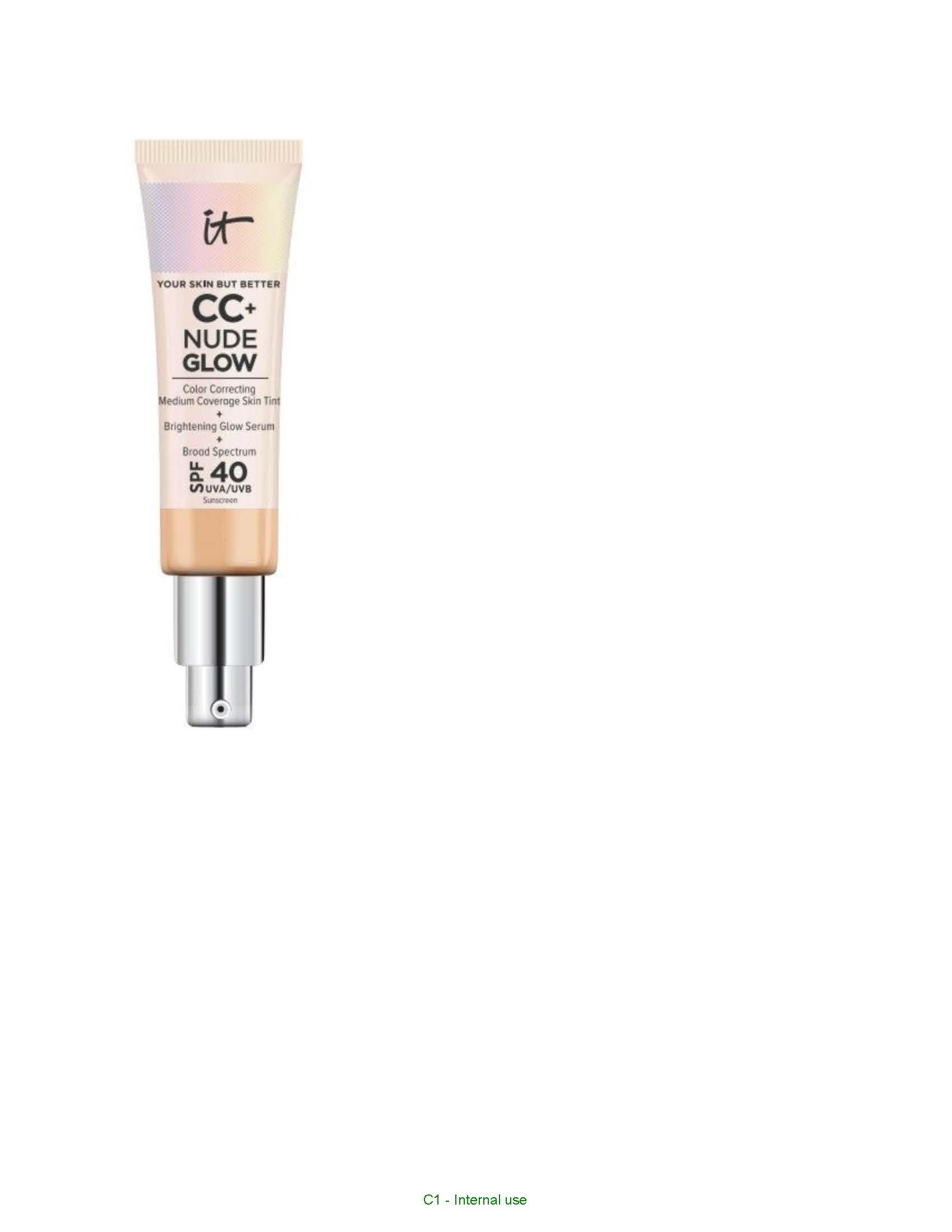 DRUG LABEL: IT COSMETICS YOUR SKIN BUT BETTER CC PLUS NUDE GLOW Color Correcting Medium Coverage Skin Tint plus Brightening Glow Serum plus Broad Spectrum SPF 40 Sunscreen
NDC: 49967-964 | Form: LIQUID
Manufacturer: L'Oreal USA Products Inc
Category: otc | Type: HUMAN OTC DRUG LABEL
Date: 20240628

ACTIVE INGREDIENTS: HOMOSALATE 73 mg/1 mL; OCTISALATE 50 mg/1 mL; OCTOCRYLENE 60 mg/1 mL
INACTIVE INGREDIENTS: WATER; GLYCERIN; CAPRYLYL TRISILOXANE; DIMETHICONE; BUTYLOCTYL SALICYLATE; NIACINAMIDE; PROPANEDIOL; DIMETHICONE/PEG-10/15 CROSSPOLYMER; PHENOXYETHANOL; SODIUM CHLORIDE; DISTEARDIMONIUM HECTORITE; DISODIUM STEAROYL GLUTAMATE; CHLORPHENESIN; CAPRYLYL GLYCOL; TRISODIUM ETHYLENEDIAMINE DISUCCINATE; LIMONENE, (+)-; MALTODEXTRIN; ALUMINUM HYDROXIDE; ADENOSINE; DIPROPYLENE GLYCOL; HYALURONATE SODIUM; CITRAL; CITRIC ACID MONOHYDRATE; LINALOOL, (+/-)-; SODIUM CITRATE; GREEN TEA LEAF; TOCOPHEROL; PENTAERYTHRITOL TETRAKIS(3-(3,5-DI-TERT-BUTYL-4-HYDROXYPHENYL)PROPIONATE); TITANIUM DIOXIDE; FERRIC OXIDE RED

Drug Facts

Active ingredients

Homosalate 7.3%

Octisalate 5%

Octocrylene 6%

Purpose

Sunscreen

Uses

- helps prevent sunburn
- if used as directed with other sun protection measures (see Directions), decreases the risk of skin cancer and early skin aging caused by the sun

Warnings

For external use only

Do not use

on damaged or broken skin

When using this product

keep our of eyes. Rinse with water to remove

Stop use and ask a doctor if

rash occurs

Keep out of reach of children.

If swallowed, get medical help or contact a Poison Control Center right away.

Directions

For sunscreen use:

- apply liberally 15 minutes before sun exposure
- reapply at least every 2 hours
- use a water resistant susncreen if swiming or sweating
- Sun Protection Measures.

Spending time in the sun increases your risk of skin cancer and early skin aging. To decrease this risk, regularly use a sunscreen with a Broad Spectrum SPF value of 15 or higher and other sun protection measures including:

- limit time in the sun, especially from 10 a.m. - 2 p.m.
- wear long-sleeved shirts, pants, hats, and sunglasses
- children under 6 months of age:

Ask a doctor

Other information

- protect the product in this container from excesssive heat and direct sun

Inactive ingredients

water, glycerin, caprylyl methicone, dimethicone, butyloctyl salicylate, cetyl PEG/PPG-10 dimethicone, niacinamide, propanediol, dimethicone/PEG-10/15 crosspolymer, synthetic fluorphlogopite, phenoxyethanol, sodium chloride
trimethylsiloxysilicate, disteardimonium hectorite, disodium stearoyl glutamate, fragrance, chlorphenesin, caprylyl glycol, silica silylate, trisodium ethylenediamine disuccinate, limonene, simethicone, maltodextrin, aluminum hydroxide, adenosine, dipropylene glycol, sodium hyaluronate, citral, citric acid, linalool, sodium citrate, camellia sinensis leaf extract, tocopherol, pentaerythrityl tetra-di-t-butyl hydroxyhydrocinnamate; may contain: titanium dioxide, iron oxides

Questions or comments?

Call 800-620-3950